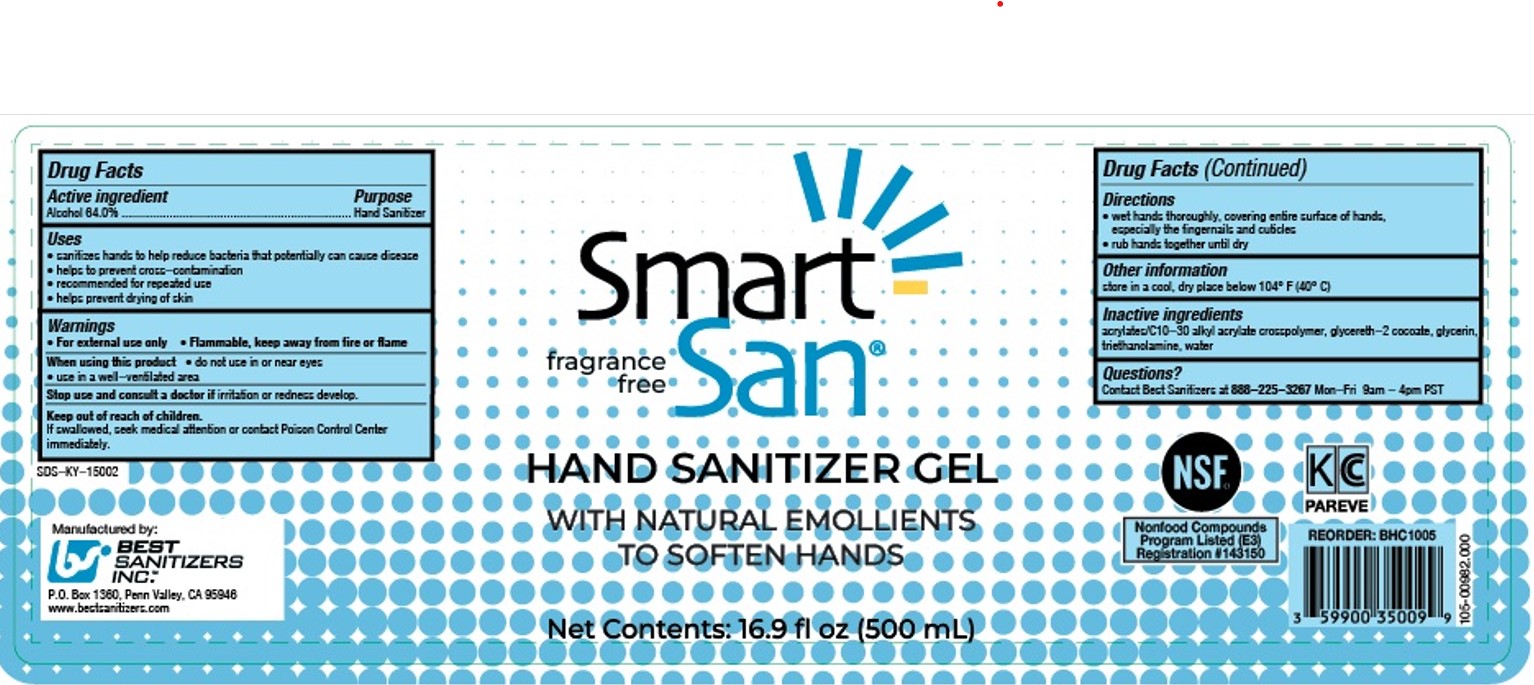 DRUG LABEL: Smart San Hand Sanitizer
NDC: 59900-121 | Form: GEL
Manufacturer: Best Sanitizers, Inc.
Category: otc | Type: HUMAN OTC DRUG LABEL
Date: 20241212

ACTIVE INGREDIENTS: ALCOHOL 64 mL/100 mL
INACTIVE INGREDIENTS: GLYCERETH-2 COCOATE; TROLAMINE; WATER; GLYCERIN; ACRYLATES/C10-30 ALKYL ACRYLATE CROSSPOLYMER (60000 MPA.S)

Smart San HSG 59900-121

Active ingredient

Alcohol 64.0%

Purpose

Hand Sanitizer

Uses

- sanitizes hands to help reduce bacteria that potentially can cause disease
- helps tp prevent cross-contamination
- recommended for repeated use
- helps prevent drying of hands

Warnings

- For external use only
- Flammable, keep away from fire or flame

When using this product

- do not use in or near eyes
- use in a well-ventilated area

Stop use and consult a doctor if irritation or redness develops.

Keep out of reach of children.

If swallowed, seek medical attention or contact Poison Control Center immediately.

Directions

- wet hands thoroughly, covering entire surface of hands, especially the fingernails and cuticles
- rub hands togetrher until dry

Other information

store in a cool, dry place below 104 F (40 C)

Inactive ingredients

acrylates/C10-30 alkyl acrylate crosspolymer, glycereth-2 cocoate, glycerin, triethanolamine, water

Questions?

Contact Best Sanitizers at 888-225-3267Mon-Fri 9am-4pm PST

Directions

- wet hands thoroughly, covering entire surface of hands, especially the fingernails and cuticles
- rub hands together until dry

PACKAGE LABEL

fragrance free

Smart

San

HAND SANITIZER GEL

WITH NATURAL EMOLLIENTS

TO SOFTEN HANDS

Net Contents:16.9 fl oz (500 mL)